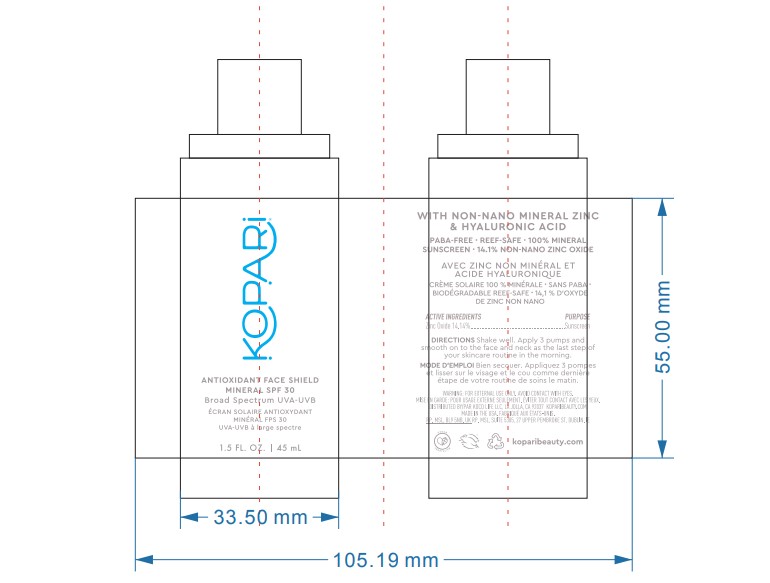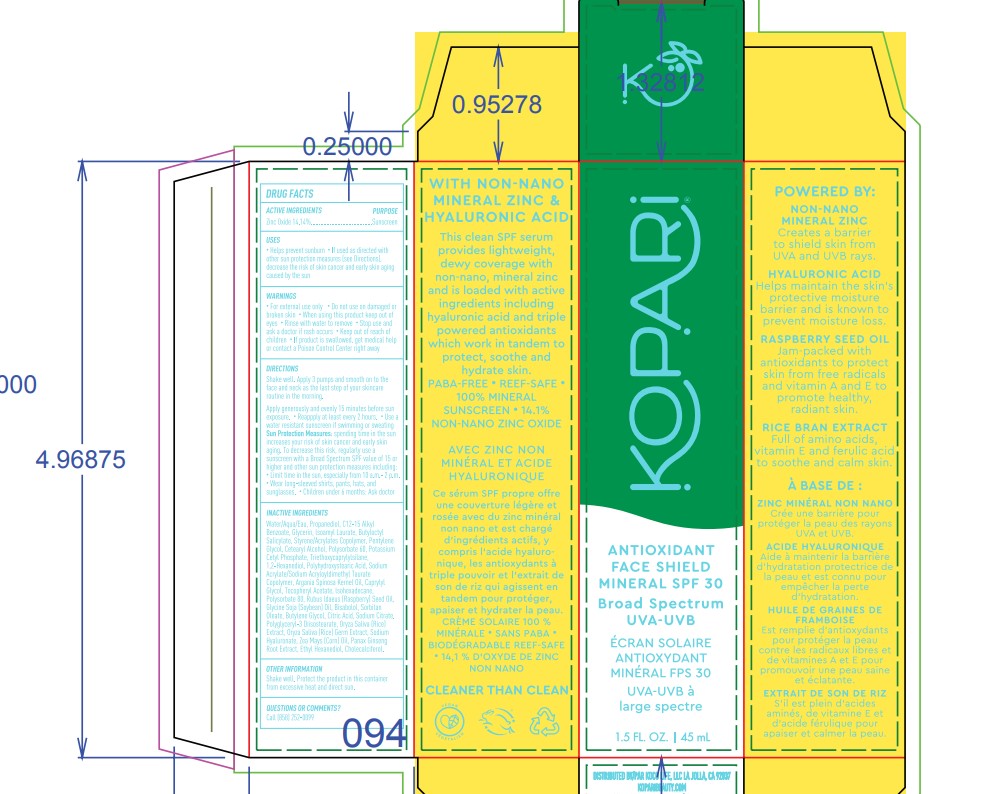 DRUG LABEL: KOPARI Antioxidant Face Shield Mineral SPF 30
NDC: 68577-154 | Form: LOTION
Manufacturer: COSMAX USA, CORPORATION
Category: otc | Type: HUMAN OTC DRUG LABEL
Date: 20241226

ACTIVE INGREDIENTS: ZINC OXIDE 14.4 mg/100 mg
INACTIVE INGREDIENTS: CORN OIL; BUTYLENE GLYCOL; CAPRYLYL GLYCOL; POLYGLYCERYL-3 DIISOSTEARATE; POLYSORBATE 80; ARGAN OIL; GLYCERIN; WATER; PROPANEDIOL; ALKYL (C12-15) BENZOATE; ISOAMYL LAURATE; BUTYLOCTYL SALICYLATE; STYRENE/ACRYLAMIDE COPOLYMER (MW 500000); PENTYLENE GLYCOL; CETOSTEARYL ALCOHOL; POLYSORBATE 60; POTASSIUM CETYL PHOSPHATE; HYALURONATE SODIUM; RUBUS IDAEUS SEED; SOYBEAN OIL; ASIAN GINSENG; ANHYDROUS CITRIC ACID; SODIUM CITRATE; ISOHEXADECANE; TRIETHOXYCAPRYLYLSILANE; LEVOMENOL; RICE GERM; SORBITAN MONOOLEATE; CHOLECALCIFEROL; 1,2-HEXANEDIOL; SODIUM ACRYLATE/SODIUM ACRYLOYLDIMETHYLTAURATE COPOLYMER (4000000 MW); POLYHYDROXYSTEARIC ACID (2300 MW); ETHOHEXADIOL

KOPARI Antioxidant Face Shield Mineral SPF 30

Active Ingredients

Zinc Oxide 14.4%

Purpose

Sunscreen

USES

- helps prevent sunburn
- if used as directed with other sun protection measures (see Directions), decreases the risk of skin cancer and early skin aging cause by the sun

Warnings

For extenal use only

Do not useon damaged or broken skin

WHEN USING

When using this productkeep out of eyes. Rinse with water to remove.

Stop use and ask a doctor ifrash occurs

Keep out of reach of children.If swallowed, get medical help or contact a Poison Control Center right away.

DIRECTIONS

- Shake well. Apply 3 pumps and smooth on to the face and neck as the last step of your skicare routine in the morning.

- Apply generously and evenly 15 minutes before sun exposure
  - Reapply at least every 2 hours.
  - Use water resistant sunscreen if swimming or sweating
  - Sun Protection Measures. Spending time in the sun increases your risk of skin cancer and early skin aging. To decrease this risk, regularly use a sunscreen with a Broad Spectrum SPF value of 15 or higher and other sun protection measures including:

- limit time in the sun, especially from 10 a.m. - 2p.m.

-wear long-sleeved shirts, pants, hats and sunglasses

Children under 6 months of age: Ask a doctor

INACTIVE INGREDIENT

Inactive ingredients: water/aqua/eau,propanediol,c12-15 alkyl benzoate,glycerin,lsoamyl laurate,butyloctyl salicylate,styrene/acrylates copolymer,pentylene glycol,cetearyl alcohol,polysorbate 60,potassium cetyl phosphate,sodium hyaluronate,rubus ldaeus (raspberry) seed oil,glycine soja (soybean) oil,oryza sativa (rice) extract, oryza sativa (rice) germ extract, panax ginseng root extract,argania spinosa kernel oil,bisabololzea mays (corn) oil,1,2-hexanediol,butylene glycol,caprylyl glycol,sodium acrylate/sodium acryloyldimethyl taurate copolymer,lsohexadecanepolyhydroxystearic acid,sodium citrate,triethoxycaprylylsilane,polyglyceryl-3 diisostearate,sorbitan oleate,citric acid,tocopheryl acetate,ethyl hexanediol,polysorbate 80,cholecalciferol

OTHER INFORMATION

Shake well. Protect the product in this container from excessive heat and direct sun

QUESTIONS or COMMENTS

Call (858) 252 0099

PACKAGE LABEL

Primary Packaging

Secondary Package